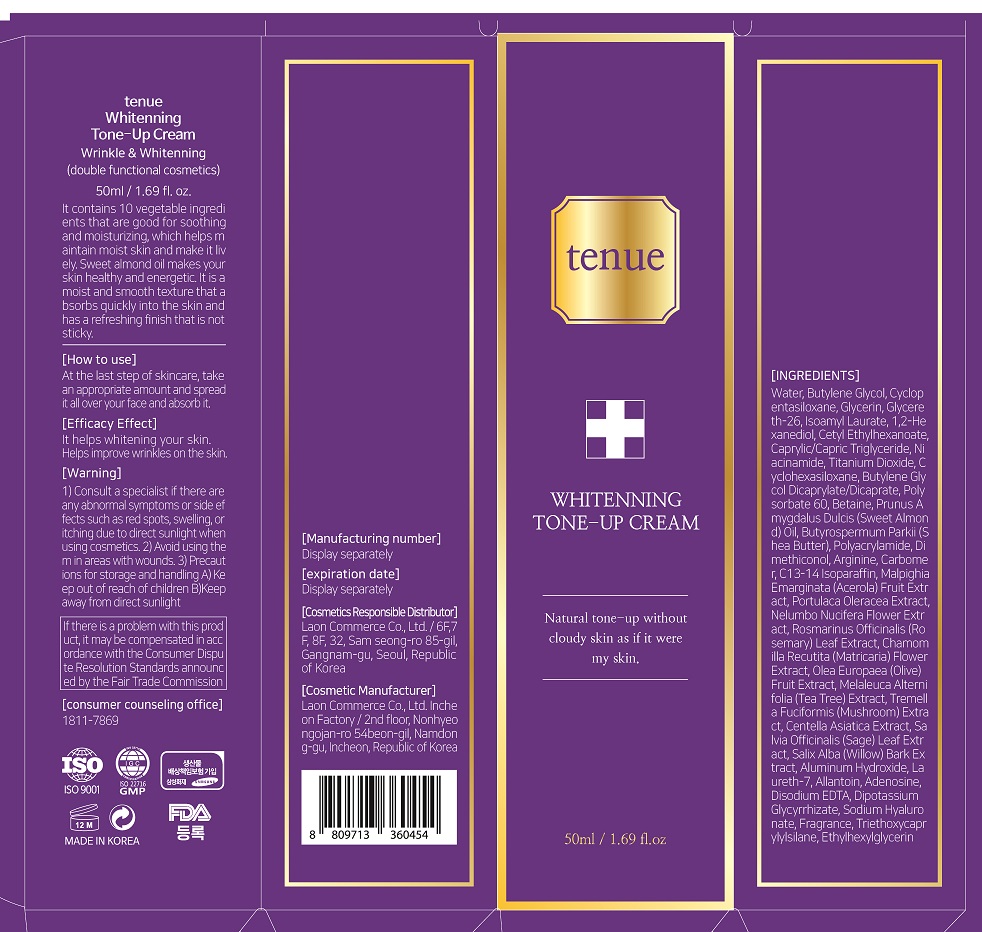 DRUG LABEL: Tenue Whitenning Tone upCream
NDC: 82083-0013 | Form: CREAM
Manufacturer: LAON COMMERCE co ltd
Category: otc | Type: HUMAN OTC DRUG LABEL
Date: 20221026

ACTIVE INGREDIENTS: ADENOSINE 0.04 g/100 mL; NIACINAMIDE 2 g/100 mL
INACTIVE INGREDIENTS: WATER

ACTIVE INGREDIENT

Adenosine, Niacinamide

INACTIVE INGREDIENT

Water
Butylene Glycol
Cyclopentasiloxane
Glycerin
Glycereth-26
Isoamyl Laurate
1,2-Hexanediol
Cetyl Ethylhexanoate
Caprylic/Capric Triglyceride
Niacinamide
Titanium Dioxide
Cyclohexasiloxane
Butylene Glycol Dicaprylate/Dicaprate
Polysorbate 60
Betaine
Prunus Amygdalus Dulcis (Sweet Almond) Oil
Butyrospermum Parkii (Shea Butter)
Polyacrylamide
Dimethiconol
Arginine
Carbomer
C13-14 Isoparaffin
Malpighia Emarginata (Acerola) Fruit Extract
Portulaca Oleracea Extract
Nelumbo Nucifera Flower Extract
Rosmarinus Officinalis (Rosemary) Leaf Extract
Chamomilla Recutita (Matricaria) Flower Extract
Olea Europaea (Olive) Fruit Extract
Melaleuca Alternifolia (Tea Tree) Extract
Tremella Fuciformis (Mushroom) Extract
Centella Asiatica Extract
Salvia Officinalis (Sage) Leaf Extract
Salix Alba (Willow) Bark Extract
Aluminum Hydroxide
Laureth-7
Allantoin
Adenosine
Disodium EDTA
Dipotassium Glycyrrhizate
Sodium Hyaluronate
Fragrance
Triethoxycaprylylsilane
Ethylhexylglycerin

PURPOSE

whitening, wrinkle care

KEEP OUT OF REACH OF THE CHILDREN

INDICATIONS AND USAGE

At the last step of skincare, take an appropriate amount and spread it all over your face and absorb it

WARNINGS

1. consult a specialist if there are any abnormal symptoms or side effects such as red spots, swelling, or itching due to direct sunlight when using cosmetics

2. avoid using them in areas with wounds

3. precautions for storage and handling

a) keep out of reach of childrea

b) keep away from direct sunlight

DOSAGE AND ADMINISTRATION

topical use only